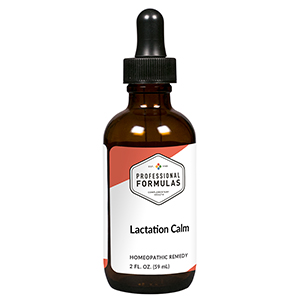 DRUG LABEL: Lactation Calm
NDC: 63083-2150 | Form: LIQUID
Manufacturer: Professional Complementary Health Formulas
Category: homeopathic | Type: HUMAN OTC DRUG LABEL
Date: 20190815

ACTIVE INGREDIENTS: ARTEMISIA ANNUA FLOWERING TOP 3 [hp_X]/59 mL; BOS TAURUS HYPOTHALAMUS 6 [hp_X]/59 mL; BOS TAURUS LYMPH VESSEL 6 [hp_X]/59 mL; SUS SCROFA MAMMARY GLAND 6 [hp_X]/59 mL; BOS TAURUS PITUITARY GLAND, POSTERIOR 6 [hp_X]/59 mL; SILICON DIOXIDE 6 [hp_X]/59 mL; AMARYLLIS BELLADONNA WHOLE 9 [hp_X]/59 mL; BRYONIA ALBA ROOT 9 [hp_X]/59 mL; URTICA URENS WHOLE 9 [hp_X]/59 mL; CONIUM MACULATUM FLOWERING TOP 12 [hp_X]/59 mL; CANIS LUPUS FAMILIARIS MILK 12 [hp_X]/59 mL; PHYTOLACCA AMERICANA ROOT 12 [hp_X]/59 mL
INACTIVE INGREDIENTS: ALCOHOL; WATER

C150

ACTIVE INGREDIENTS

Chamomilla 3X
Hypothalamus 6X
Lymph 6X
Mammary 6X
Pituitary 6X
Silicea 6X
Belladonna 9X
Bryonia 9X
Urtica urens 9X
Conium maculatum 12X
Lac caninum 12X
Phytolacca decandra 12X

QUESTIONS

Professional Formulas

PO Box 2034 Lake Oswego, OR 97035

INDICATIONS

For temporary assistance with excessive lactation.*

PURPOSE

*Claims based on traditional homeopathic practice, not accepted medical evidence. Not FDA evaluated.

WARNINGS

In case of overdose, get medical help or contact a poison control center right away.

Keep out of the reach of children.

PREGNANCY OR BREAST FEEDING

If pregnant or breastfeeding, ask a healthcare professional before use.

DIRECTIONS

Place drops under tongue 30 minutes before/after meals. Adults and children 12 years and over: Take 10 drops up to 3 times per day. Consult a physician for use in children under 12 years of age.

OTHER INFORMATION

Tamper resistant. If seal is broken, do not use. After opening, close container tightly and store at room temperature away from heat.

INACTIVE INGREDIENTS

20% ethanol, purified water.

LABEL

Est 1985

Professional Formulas

Complementary Health

Lactation Calm

Homeopathic Remedy

2 FL. OZ. (59 mL)